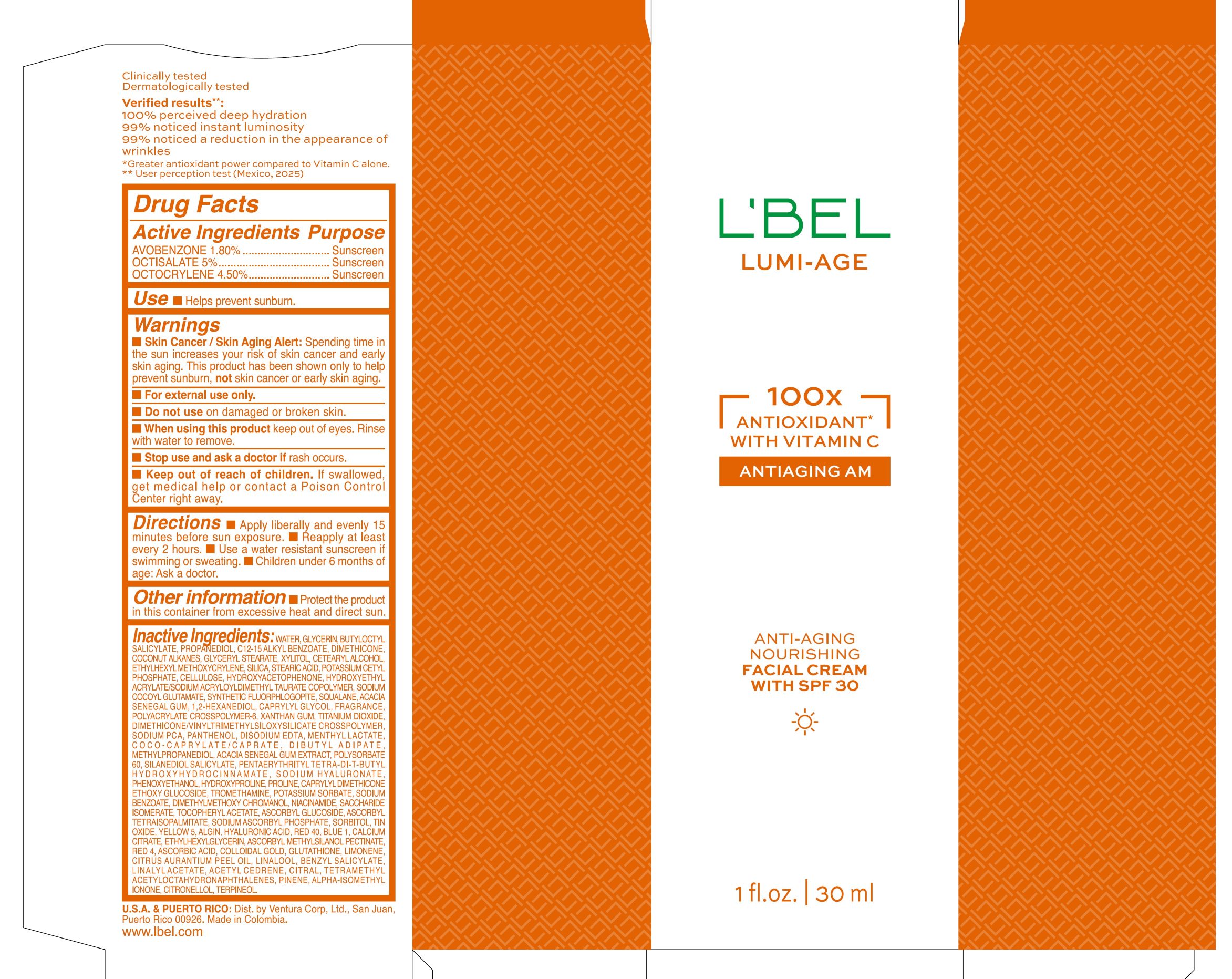 DRUG LABEL: LBEL LUMI AGE ANTI AGING NOURISHING FACIAL WITH SPF 30
NDC: 14141-465 | Form: EMULSION
Manufacturer: BEL STAR SA
Category: otc | Type: HUMAN OTC DRUG LABEL
Date: 20251203

ACTIVE INGREDIENTS: OCTISALATE 50 mg/1 mL; AVOBENZONE 18 mg/1 mL; OCTOCRYLENE 45 mg/1 mL
INACTIVE INGREDIENTS: SODIUM PCA; EDETATE DISODIUM; MENTHYL LACTATE; PHENOXYETHANOL; SODIUM BENZOATE; .ALPHA.-TOCOPHEROL ACETATE; SILICON DIOXIDE; YELLOW 5; GLUTATHIONE; LINALYL ACETATE; ASCORBYL GLUCOSIDE; SODIUM ASCORBYL PHOSPHATE; ASCORBYL METHYLSILANOL PECTINATE; LIMONENE, (+)-; TERPINEOL; BUTYLOCTYL SALICYLATE; ALGIN; LINALOOL; PANTHENOL; CITRUS AURANTIUM PEEL OIL; PROPANEDIOL; COCONUT ALKANES; TITANIUM DIOXIDE; METHYLPROPANEDIOL; PROLINE; HYALURONIC ACID; GLYCERIN; C12-15 ALKYL BENZOATE; DIMETHICONE; RED 40; STEARIC ACID; GLYCERYL STEARATE; ETHYLHEXYL METHOXYCRYLENE; WATER; TIN OXIDE; SODIUM COCOYL GLUTAMATE; POLYACRYLATE CROSSPOLYMER-6; POWDERED CELLULOSE; HYDROXYACETOPHENONE; SACCHARIDE ISOMERATE; POTASSIUM CETYL PHOSPHATE; ACACIA SENEGAL GUM; XYLITOL; SQUALANE; CAPRYLYL DIMETHICONE ETHOXY GLUCOSIDE; POLYSORBATE 60; ACETYL CEDRENE; TETRAMETHYL ACETYLOCTAHYDRONAPHTHALENES; PINENE; CITRONELLOL; COCO-CAPRYLATE/CAPRATE; DIBUTYL ADIPATE; PENTAERYTHRITYL TETRA-DI-T-BUTYL HYDROXYHYDROCINNAMATE; ASCORBYL TETRAISOPALMITATE; CAPRYLYL GLYCOL; RED 4; COLLOIDAL GOLD; ALPHA-ISOMETHYL IONONE; CETEARYL ALCOHOL; BLUE 1; CALCIUM CITRATE; SILANEDIOL SALICYLATE; TROMETHAMINE; POTASSIUM SORBATE; DIMETHYLMETHOXY CHROMANOL; NIACINAMIDE; SORBITOL; HYDROXYETHYL ACRYLATE/SODIUM ACRYLOYLDIMETHYL TAURATE COPOLYMER (45000 MPA.S AT 1%); ETHYLHEXYLGLYCERIN; BENZYL SALICYLATE; 1,2-HEXANEDIOL; XANTHAN GUM; CITRAL; ASCORBIC ACID; SODIUM HYALURONATE; HYDROXYPROLINE

LBEL LUMI AGE ANTI AGING NOURISHING FACIAL WITH SPF 30

Active Ingredients

AVOBENZONE 1.80%

OCTISALATE 5%

OCTOCRYLENE 4.50%

Purpose

Sunscreen

Use

- Helps prevent sunburn.

Warnings

- Skin Cancer/Skin Aging Alert: Spending time in the sun increases your risk of skin cancer and early skin aging. This product has been shown only to help prevent sunburn, not skin cancer or early skin aging.
- For external use only.

Do not use

on damaged or broken skin.

When using this product

keep out of eyes. Rinse with water to remove.

Stop use and ask a doctor if

rash occurs.

Keep out of reach of children.

If swallowed, get medical help or contact a Poison Control Center right away.

Directions

- Apply liberally and evenly 15 minutes before sun exposure.
- Reapply at least every 2 hours.
- Use a water resistant sunscreen if swimming or sweating.
- Children under 6 months of age: Ask a doctor.

Other information

- Protect the product in this container from excessive heat and direct sun.

Inactive Ingredients

WATER, GLYCERIN, BUTYLOCTYL SALICYLATE, PROPANEDIOL, C12-15 ALKYL BENZOATE, DIMETHICONE, COCONUT ALKANES, GLYCERYL STEARATE, XYLITOL, CETEARYL ALCOHOL, ETHYLHEXYL METHOXYCRYLENE, SILICA, STEARIC ACID, POTASSIUM CETYL PHOSPHATE, CELLULOSE, HYDROXYACETOPHENONE, HYDROXYETHYL ACRYLATE/SODIUM ACRYLOYLDIMETHYL TAURATE COPOLYMER, SODIUM COCOYL GLUTAMATE, SYNTHETIC FLUORPHLOGOPITE, SQUALANE, ACACIA SENEGAL GUM, 1,2-HEXANEDIOL, CAPRYLYL GLYCOL, FRAGRANCE, POLYACRYLATE CROSSPOLYMER-6, XANTHAN GUM, TITANIUM DIOXIDE, DIMETHICONE/VINYLTRIMETHYLSILOXYSILICATE CROSSPOLYMER, SODIUM PCA, PANTHENOL, DISODIUM EDTA, MENTHYL LACTATE, COCO-CAPRYLATE/CAPRATE, DIBUTYL ADIPATE, METHYLPROPANEDIOL, ACACIA SENEGAL GUM EXTRACT, POLYSORBATE 60, SILANEDIOL SALICYLATE, PENTAERYTHRITYL TETRA-DI-T-BUTYL HYDROXYHYDROCINNAMATE, SODIUM HYALURONATE, PHENOXYETHANOL, HYDROXYPROLINE, PROLINE, CAPRYLYL DIMETHICONE ETHOXY GLUCOSIDE, TROMETHAMINE, POTASSIUM SORBATE, SODIUM BENZOATE, DIMETHYLMETHOXY CHROMANOL, NIACINAMIDE, SACCHARIDE ISOMERATE, TOCOPHERYL ACETATE, ASCORBYL GLUCOSIDE, ASCORBYL TETRAISOPALMITATE, SODIUM ASCORBYL PHOSPHATE, SORBITOL, TIN OXIDE, YELLOW 5, ALGIN, HYALURONIC ACID, RED 40, BLUE 1, CALCIUM CITRATE, ETHYLHEXYLGLYCERIN, ASCORBYL METHYLSILANOL PECTINATE, RED 4, ASCORBIC ACID, COLLOIDAL GOLD, GLUTATHIONE, LIMONENE, CITRUS AURANTIUM PEEL OIL, LINALOOL, BENZYL SALICYLATE, LINALYL ACETATE, ACETYL CEDRENE, CITRAL, TETRAMETHYL ACETYLOCTAHYDRONAPHTHALENES, PINENE, ALPHA-ISOMETHYL IONONE, CITRONELLOL, TERPINEOL.